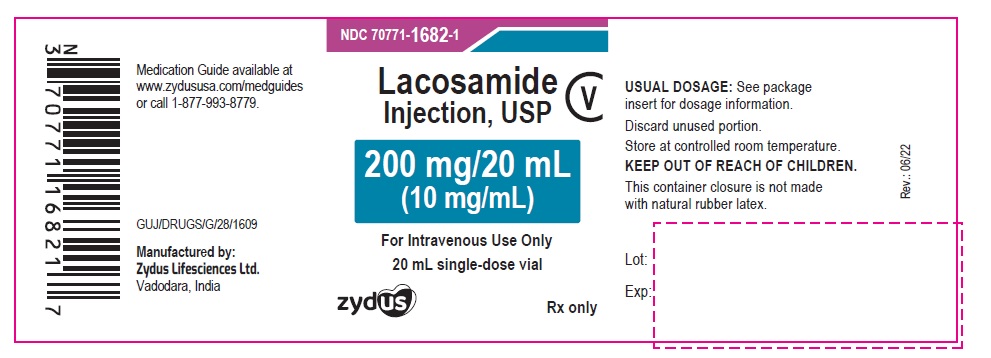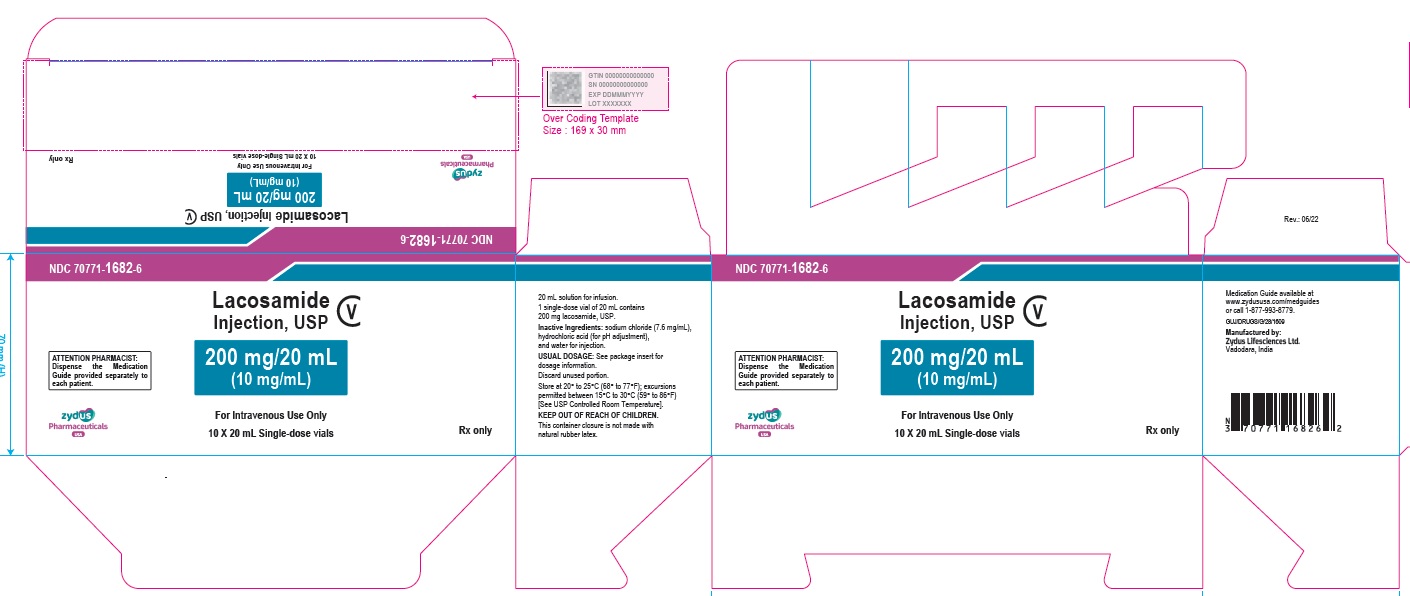 DRUG LABEL: LACOSAMIDE
NDC: 70771-1682 | Form: INJECTION
Manufacturer: Zydus Lifesciences Limited
Category: prescription | Type: HUMAN PRESCRIPTION DRUG LABEL
Date: 20231003
DEA Schedule: CV

ACTIVE INGREDIENTS: LACOSAMIDE 10 mg/1 mL
INACTIVE INGREDIENTS: HYDROCHLORIC ACID; SODIUM CHLORIDE; WATER

LACOSAMIDE injection, for intravenous use, CV

PACKAGE LABEL.PRINCIPAL DISPLAY PANEL

NDC 70771-1682-1

Lacosamide Injection, USP 200 mg/20 mL (10 mg/mL); CV

For Intravenous Use Only

20 mL single-dose vial

Rx only

NDC 70771-1682-6

Lacosamide Injection, USP 200 mg/20 mL (10 mg/mL); CV

For Intravenous Use Only

10 X 20 mL Single-dose vials

Rx only